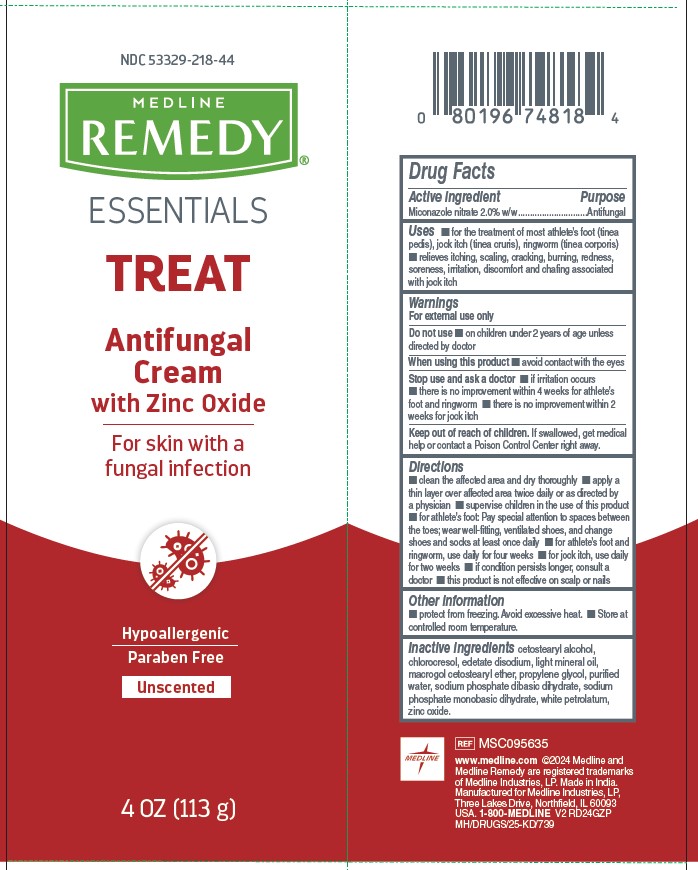 DRUG LABEL: Medline
NDC: 53329-218 | Form: CREAM
Manufacturer: Medline Industries, LP
Category: otc | Type: HUMAN OTC DRUG LABEL
Date: 20251106

ACTIVE INGREDIENTS: MICONAZOLE NITRATE 20 mg/100 g
INACTIVE INGREDIENTS: CHLOROCRESOL; WHITE PETROLATUM; ZINC OXIDE; SODIUM PHOSPHATE DIBASIC DIHYDRATE; LIGHT MINERAL OIL; POLYOXYL 20 CETOSTEARYL ETHER; EDETATE DISODIUM; PROPYLENE GLYCOL; WATER; SODIUM PHOSPHATE, MONOBASIC, DIHYDRATE; CETOSTEARYL ALCOHOL

218 Remedy Antifungal Cream with Zinc Oxide

Active ingredient

Miconazole nitrate 2.0% w/w

Purpose

Antifungal

Uses

- for the treatment of most athlete’s foot (tinea pedis), jock itch (tinea cruris), ringworm (tinea corporis)
- relieves itching, scaling, cracking, burning, redness, soreness, irritation, discomfort and chafing associated with jock itch

Warnings

For external use only

Do not use

- on children under 2 years of age unless directed by doctor

When using this product

- avoid contact with the eyes

Stop use and ask a doctor

- if irritation occurs
- there is no improvement within 4 weeks for athlete’s foot and ringworm
- there is no improvement within 2 weeks for jock itch

Keep out of reach of children.

If swallowed, get medical help or contact a Poison Control Center right away.

Directions

- clean the affected area and dry thoroughly
- apply a thin layer over affected area twice daily or as directed by a physician
- supervise children in the use of this product
- for athlete’s foot: Pay special attention to spaces between the toes; wear well-fitting, ventilated shoes, and change shoes and socks at least once daily
- for athlete’s foot and ringworm, use daily for four weeks
- for jock itch, use daily for two weeks
- if condition persists longer, consult a doctor
- this product is not effective on scalp or nails

Other information

- protect from freezing. Avoid excessive heat.
- Store at controlled room temperature.

Inactive ingredients

cetostearyl alcohol, chlorocresol, edetate disodium, light mineral oil, macrogol cetostearyl ether, propylene glycol, purified water, sodium phosphate dibasic dihydrate, sodium phosphate monobasic dihydrate, white petrolatum, zinc oxide.

Manufacturing information

www.medline.com ©2024 Medline and Medline Remedy are registered trademarks of Medline Industries, LP.

Made in India.

Manufactured for Medline Industries, LP,
Three Lakes Drive, Northfield, IL 60093 USA.

1-800-MEDLINE

REF: MSC095635